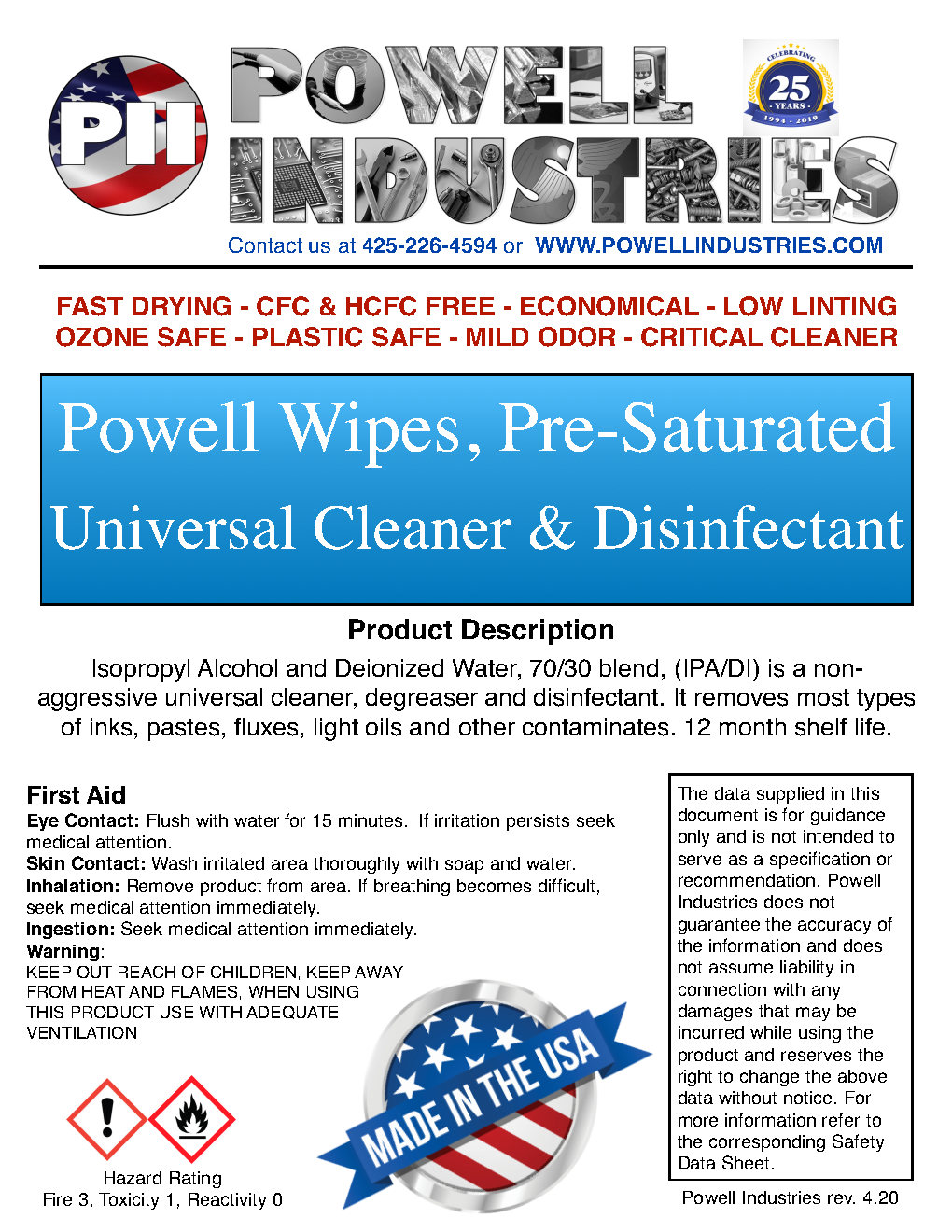 DRUG LABEL: Hand Sanitizer
NDC: 80210-001 | Form: CLOTH
Manufacturer: POWELL INDUSTRIES INC
Category: otc | Type: HUMAN OTC DRUG LABEL
Date: 20200902

ACTIVE INGREDIENTS: ISOPROPYL ALCOHOL 70 mL/100 mL
INACTIVE INGREDIENTS: WATER

hand sanitizing wipes

Active Ingredient(s)

Isopropyl Alcohol 70% v/v. Purpose: Antiseptic

Purpose

Antiseptic, Hand Sanitizer

Use

Hand Sanitizer to help reduce bacteria that potentially can cause disease. For use when soap and water are not available.

Warnings

For external use only. Flammable. Keep away from heat or flame

DO NOT FLUSH

Do not use

- in children less than 2 months of age
- on open skin wounds

When using this product use with adequate ventilation. In case of contact with eyes, rinse eyes thoroughly with water for 15 minutes.
Stop use and ask a doctor if irritation or rash occurs. These may be signs of a serious condition.
Keep out of reach of children. If swallowed, get medical help or contact a Poison Control Center right away.

Stop use and ask a doctor if irritation or rash occurs. These may be signs of a serious condition.

Keep out of reach of children. If swallowed, get medical help or contact a Poison Control Center right away.

Directions

- wipe asneeded

Other information

- Store between 15-30C (59-86F)
- Avoid freezing and excessive heat above 40C (104F)

Inactive ingredients

deionized water

Package Label - Principal Display Panel

226 ml NDC: 80210-001-01